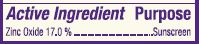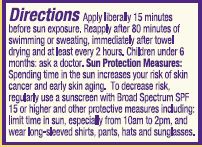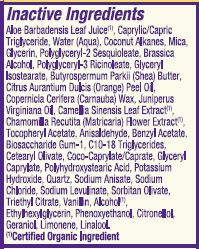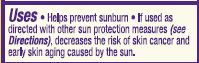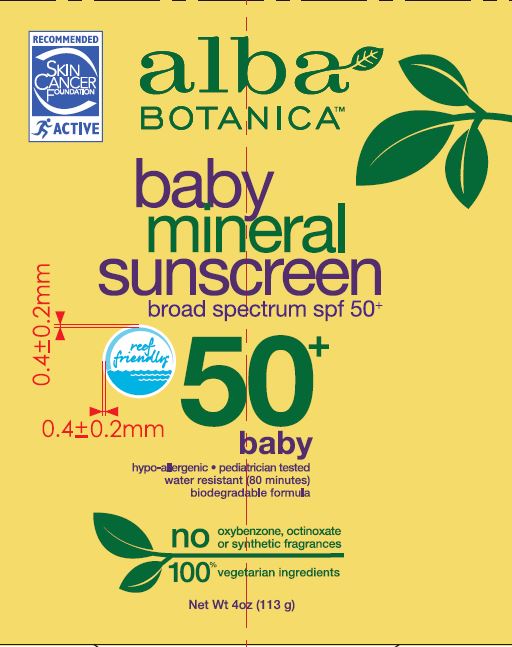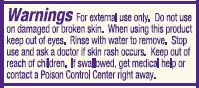 DRUG LABEL: Baby Mineral SPF 50
NDC: 61995-0437 | Form: LOTION
Manufacturer: The Hain Celestial Group, Inc.
Category: otc | Type: HUMAN OTC DRUG LABEL
Date: 20210205

ACTIVE INGREDIENTS: ZINC OXIDE 17 g/100 g
INACTIVE INGREDIENTS: JUNIPERUS VIRGINIANA OIL; O-ANISALDEHYDE; CETEARYL OLIVATE; GLYCERYL CAPRYLATE; SODIUM CHLORIDE; SODIUM LEVULINATE; GLYCERYL ISOSTEARATE; COCO-CAPRYLATE/CAPRATE; GREEN TEA LEAF; POLYGLYCERYL-3 RICINOLEATE; SHEA BUTTER; CARNAUBA WAX; .ALPHA.-TOCOPHEROL ACETATE; POLYHYDROXYSTEARIC ACID (2300 MW); SODIUM ANISATE; VANILLIN; .BETA.-CITRONELLOL, (+/-)-; ALCOHOL; LINALOOL, (+/-)-; GERANIOL; SORBITAN OLIVATE; TRIETHYL CITRATE; ETHYLHEXYLGLYCERIN; PHENOXYETHANOL; BIOSACCHARIDE GUM-1; ORANGE OIL; CHAMOMILE; BENZYL ACETATE; C10-18 TRIGLYCERIDES; MEDIUM-CHAIN TRIGLYCERIDES; WATER; POLYGLYCERYL-2 SESQUIOLEATE; POTASSIUM HYDROXIDE; COCONUT ALKANES; ALOE VERA LEAF; MICA; GLYCERIN; LIMONENE, (+/-)-

AL00437 Baby Mineral SPF 50+